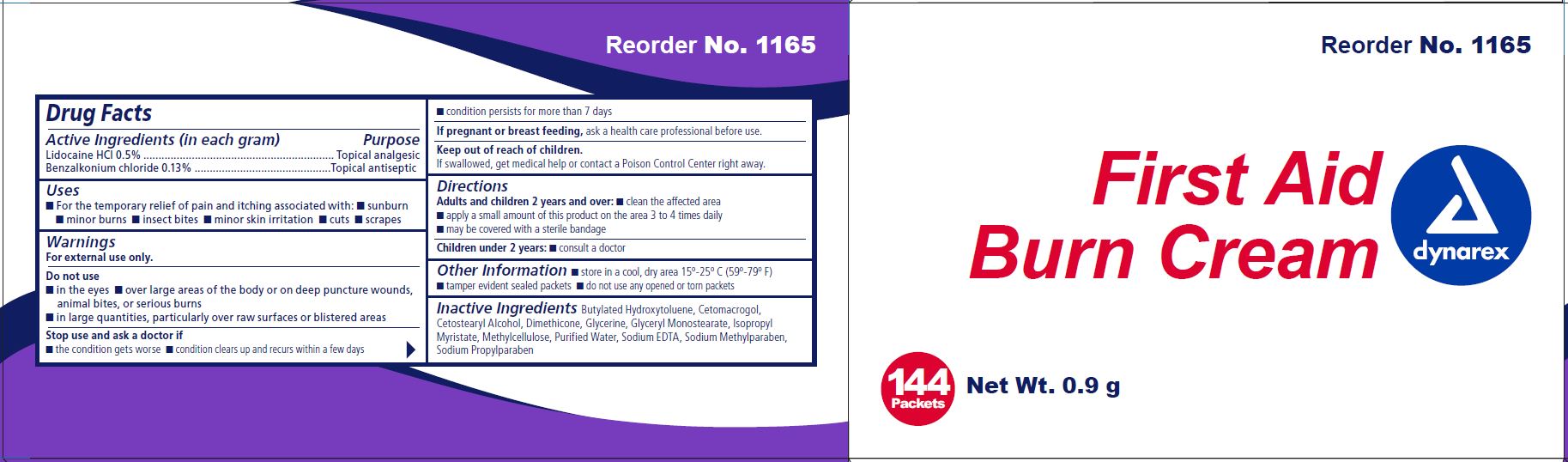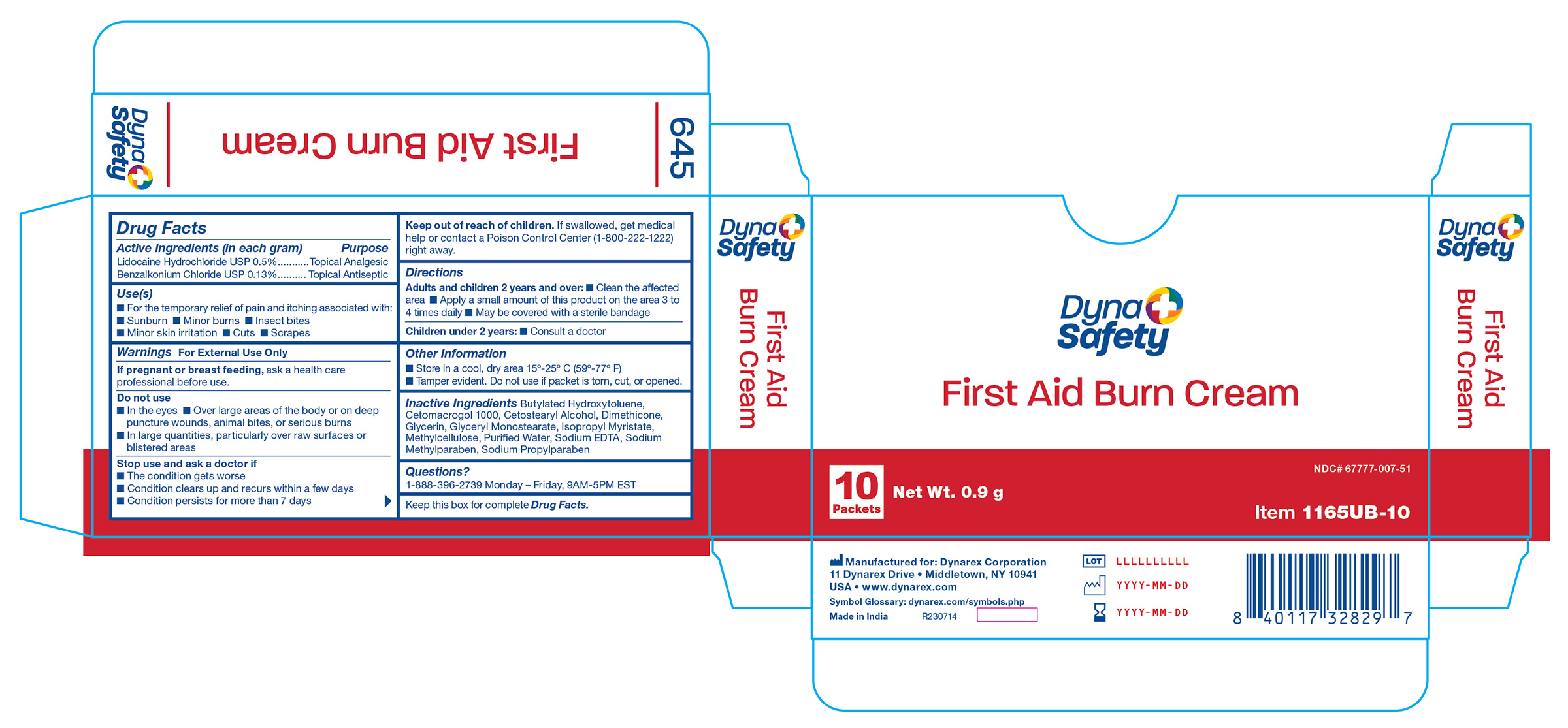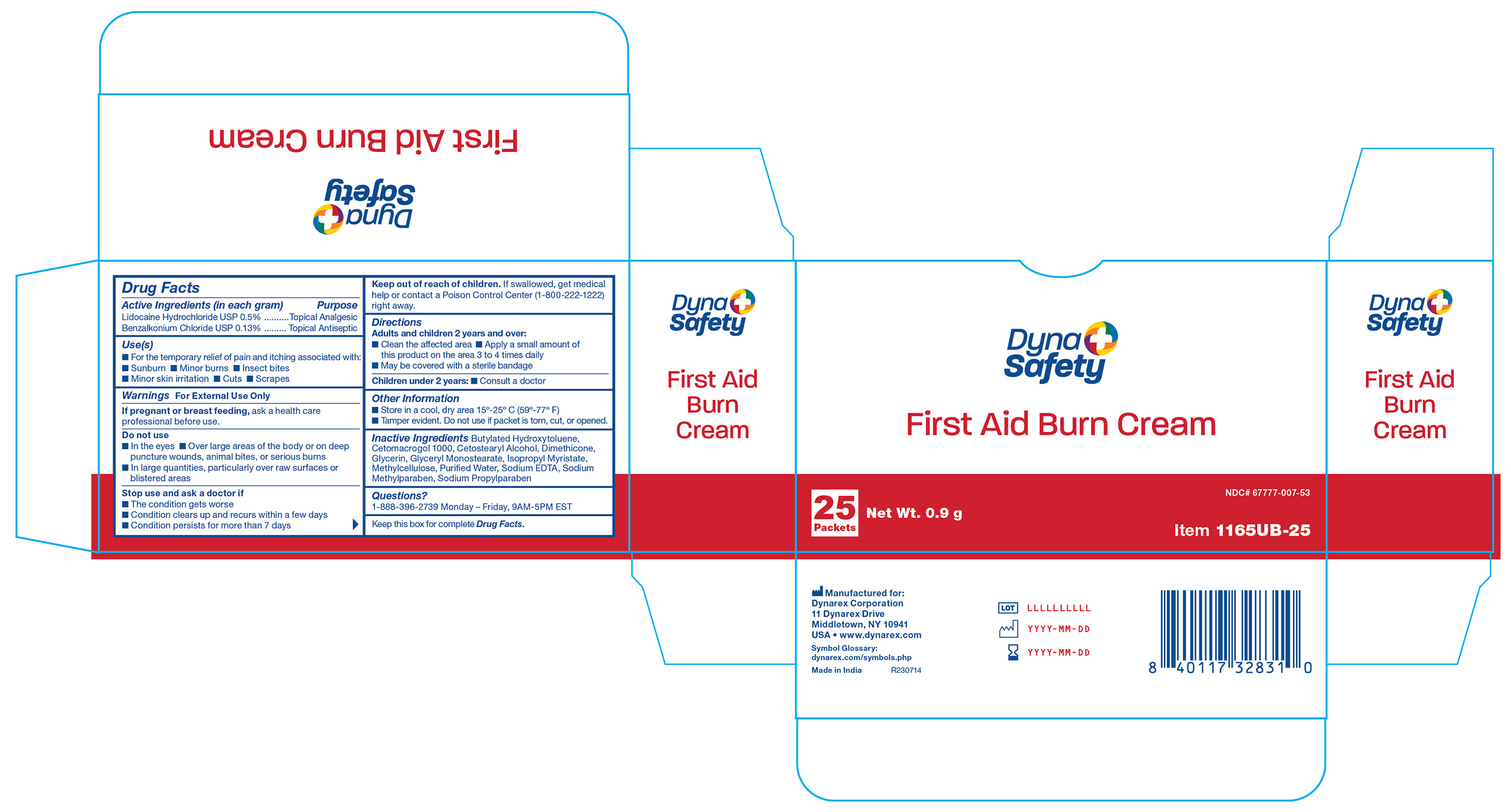 DRUG LABEL: Burn First Aid
NDC: 67777-007 | Form: CREAM
Manufacturer: Dynarex Corporation
Category: otc | Type: HUMAN OTC DRUG LABEL
Date: 20240122

ACTIVE INGREDIENTS: LIDOCAINE HYDROCHLORIDE 50 mg/10000 mg; BENZALKONIUM CHLORIDE 13 mg/10000 mg
INACTIVE INGREDIENTS: BUTYLATED HYDROXYTOLUENE; EDETATE SODIUM; METHYLPARABEN SODIUM; PROPYLPARABEN SODIUM; CETETH-20; METHYLCELLULOSE (4000 CPS); ISOPROPYL MYRISTATE; WATER; CETOSTEARYL ALCOHOL; GLYCERIN; GLYCERYL MONOSTEARATE; DIMETHICONE 350

1165 First Aid Burn Cream NDC 67777-007-50
1165UB-10 First Aid Burn Cream NDC 67777-007-52
1165UB-25 First Aid Burn Cream NDC 67777-007-54

Active Ingredient

Lidocaine HCl 0.5%

Purpose

Topical analgesic

Active Ingredient

Benzalkonium chloride 0.13%

Purpose

Topical antiseptic

Uses

For the temporary relief of pain and itching associated with sunburn, minor burns, insect bites, minor skin irritation, cuts, scrapes

Warnings

For external use only

Do not use

- in the eyes
- over large areas of the body or on deep puncture wounds, animal bites, or serious burns
- in large quantities, particularly over raw surfaces or blistered areas

Stop use and ask a doctor if

- the condition gets worse
- condition clears up and recurs within a few days
- condition persists for more than 7 days

If pregnant or breast feeding,

ask a health care professional before use.

KEEP OUT OF REACH OF CHILDREN

If swallowed, get medical help or contact a Poison Control Center right away.

Directions

Adults and children 2 years and over:

- clean the affected area
- apply a small amount of this product on the area 3 to 4 times daily
- may be covered with a sterile bandage

Children under 2 years:

- consult a doctor

Other Information

- store in a cool, dry area 15°-25° C (59°-79° F)
- tamper evident sealed packets
- do not use any opened or torn packets

Inactive Ingredients

Butylated Hydroxytoluene, Cetomacrogol, Cetostearyl Alcohol, Dimethicone, Glycerine, Glyceryl Monostearate, Isopropyl Myristate, Methylcellulose, Purified Water, Sodium EDTA, Sodium Methylparaben, Sodium Propylparaben

1165UB-10 Label

1165UB-10